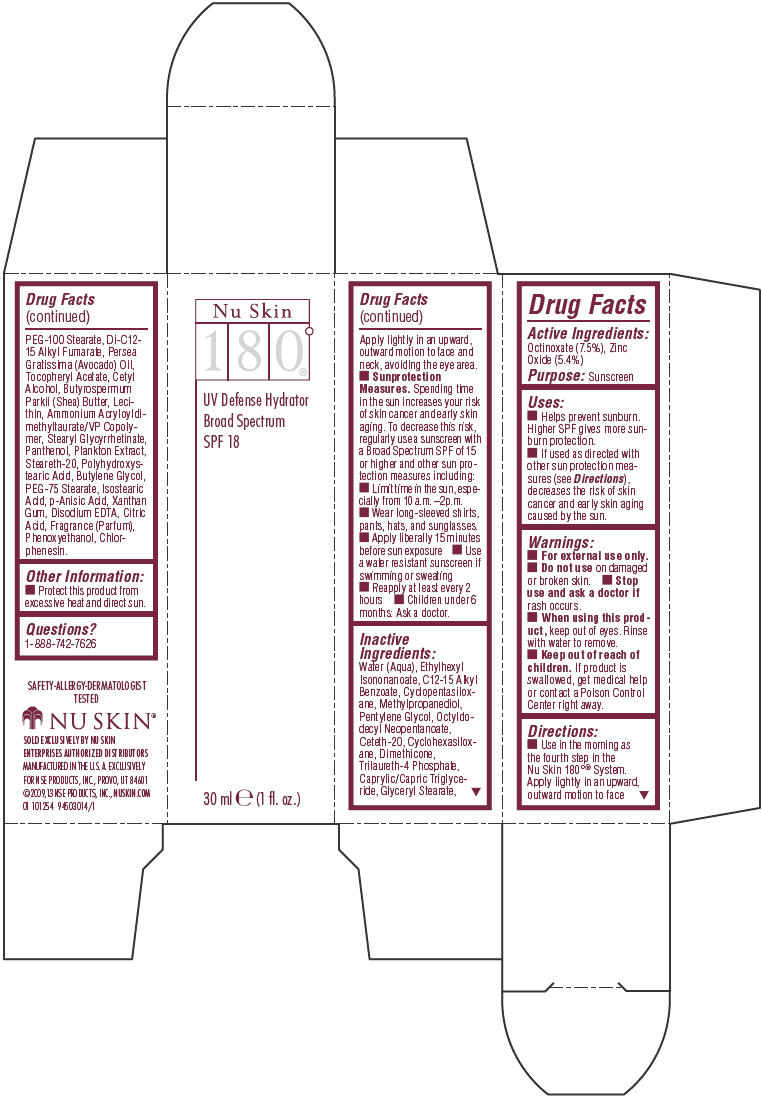 DRUG LABEL: Nu Skin 180 Degree UV Defense Hydrator SPF 18
NDC: 62839-1254 | Form: LOTION
Manufacturer: NSE Products, Inc.
Category: otc | Type: HUMAN OTC DRUG LABEL
Date: 20241224

ACTIVE INGREDIENTS: Octinoxate 75 mg/1 mL; Zinc Oxide 54 mg/1 mL
INACTIVE INGREDIENTS: Water; Ethylhexyl Isononanoate; Alkyl (C12-15) Benzoate; Cyclomethicone 5; Methylpropanediol; Pentylene Glycol; Octyldodecyl Neopentanoate; Ceteth-20; Cyclomethicone 6; Dimethicone; Trilaureth-4 Phosphate; Medium-Chain Triglycerides; Glyceryl Monostearate; PEG-100 Stearate; Di-C12-15 Alkyl Fumarate; Avocado Oil; Shea Butter; Ammonium Acryloyldimethyltaurate/VP Copolymer; Stearyl Glycyrrhetinate; Panthenol; Steareth-20; Butylene Glycol; PEG-75 Stearate; Isostearic Acid; p-Anisic Acid; Xanthan Gum; Edetate Disodium; Citric Acid Monohydrate; Phenoxyethanol; Chlorphenesin

Nu Skin 180°® UV Defense Hydrator SPF 18

Drug Facts

Active Ingredients

Octinoxate (7.5%), Zinc Oxide (5.4%)

Purpose

Sunscreen

Uses

- Helps prevent sunburn. Higher SPF gives more sunburn protection.
- If used as directed with other sun protection measures (see Directions), decreases the risk of skin cancer and early skin aging caused by the sun.

Warnings

- For external use only.

- Do not use on damaged or broken skin.

- Stop use and ask a doctor if rash occurs.

- When using this product, keep out of eyes. Rinse with water to remove.

- Keep out of reach of children. If product is swallowed, get medical help or contact a Poison Control Center right away.

Directions

- Use in the morning as the fourth step in the Nu Skin 180°® System. Apply lightly in an upward, outward motion to face
  Apply lightly in an upward, outward motion to face and neck, avoiding the eye area.
- Sunprotection Measures. Spending time in the sun increases your risk of skin cancer and early skin aging. To decrease this risk, regularly use a sunscreen with a Broad Spectrum SPF of 15 or higher and other sun protection measures including:
  - Limit time in the sun, especially from 10 a.m. –2p.m.
  - Wear long-sleeved shirts, pants, hats, and sunglasses.
  - Apply liberally 15 minutes before sun exposure
  - Use a water resistant sunscreen if swimming or sweating
  - Reapply at least every 2 hours
- Children under 6 months: Ask a doctor.

Inactive Ingredients

Water (Aqua), Ethylhexyl Isononanoate, C12-15 Alkyl Benzoate, Cyclopentasiloxane, Methylpropanediol, Pentylene Glycol, Octyldodecyl Neopentanoate, Ceteth-20, Cyclohexasiloxane, Dimethicone, Trilaureth-4 Phosphate, Caprylic/Capric Triglyceride, Glyceryl Stearate, PEG-100 Stearate, Di-C12-15 Alkyl Fumarate, Persea Gratissima (Avocado) Oil, Tocopheryl Acetate, Cetyl Alcohol, Butyrospermum Parkii (Shea) Butter, Lecithin, Ammonium Acryloyldimethyltaurate/VP Copolymer, Stearyl Glycyrrhetinate, Panthenol, Plankton Extract, Steareth-20, Polyhydroxystearic Acid, Butylene Glycol, PEG-75 Stearate, Isostearic Acid, p-Anisic Acid, Xanthan Gum, Disodium EDTA, Citric Acid, Fragrance (Parfum), Phenoxyethanol, Chlorphenesin.

Other Information

- Protect this product from excessive heat and direct sun.

Questions?

1-888-742-7626

PRINCIPAL DISPLAY PANEL - 30 ml Bottle Carton

Nu Skin
180°®

UV Defense Hydrator
Broad Spectrum
SPF 18

30 ml e (1 fl. oz.)